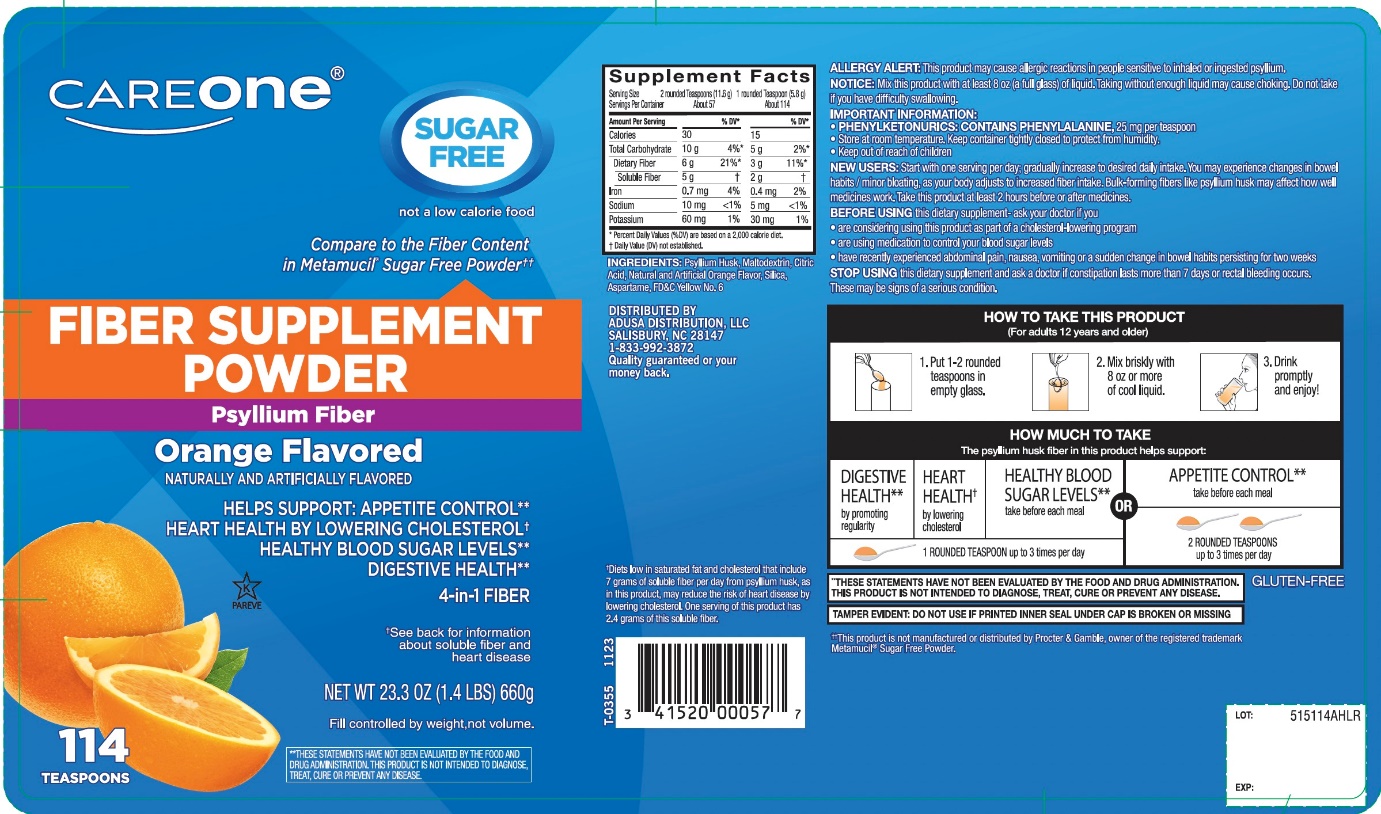 DRUG LABEL: CAREONE

NDC: 41520-515 | Form: POWDER
Manufacturer: FOODHOLD USA
Category: otc | Type: HUMAN OTC DRUG LABEL
Date: 20250718

ACTIVE INGREDIENTS: PSYLLIUM HUSK 3.4 g/5.8 g
INACTIVE INGREDIENTS: ASPARTAME; ANHYDROUS CITRIC ACID; FD&C YELLOW NO. 6; MALTODEXTRIN; SILICON DIOXIDE

CAREONE Fiber Supplement Orange Flavor Sugar free

Drug Facts

Active ingredient: (in each TEASPOON)

Psyllium husk approximately 3.4 g

Purpose

Bulk-forming Laxative

Uses:

- for relief of occasional constipation (irregularity)
- generally produces bowel movement in 12-72 hours

Warnings:

Choking:

Taking this product without adequate fluid may cause it to swell and block your throat or esophagus and may cause choking. Do not take this product if you have difficulty in swallowing. If you experience chest pain, vomiting, or difficulty in swallowing or breathing after taking this product, seek immediate medical attention.

Allergy alert:

This product may cause allergic reaction in people sensitive to inhaled or ingested psyllium.

Ask a doctor before use if you have

- a sudden change in bowel habits persisting for 2 weeks
- abdominal pain, nausea or vomiting

Stop use and ask a doctor if

- constipation lasts more than 7 days
- rectal bleeding occurs

These may be signs of a serious condition.

Keep out of reach of children.In case of overdose, get medical help or contact a Poison Control Center right away at 1-800-222-1222.

Directions:

Put one dose into an empty glass. Mix this product (child or adult dose) with at least 8 ounces (a full glass) of water or other fluid. Taking this product without enough liquid may cause choking. See choking warning. Stir briskly and drink promptly. If mixture thickens, add more liquid and stir.

Adults & Children 12 years & older: | 1 rounded TEASPOON in 8 ounces of liquid at the first sign of irregularity. Can be taken up to 3 times daily.
Children 6-11 yrs : | ½ adult dose in 8 ounces of liquid, up to 3 times daily
Children under 6 yrs: | Consult a doctor

Bulk forming fibers like psyllium husk may affect how well other medicines work. If you are taking a prescription medicine by mouth, take this product at least 2 hours before or 2 hours after the prescribed medicine. As your body adjusts to increased fiber intake, you may experience changes in bowel habits or minor bloating.

New Users

Start with 1 serving per day; gradually increased to desired daily intake. You may initially experience changes in bowel habits or minor bloating, as your body adjusts to increased fiber intake.

Other information:

- each teaspoon contains : potassium 35 mg; sodium 5 mg
- PHENYLKETONURICS: CONTAINS PHENYLALANINE,25 mg per teaspoon
- contains a 100% natural, therapeutic fiber
- store at room temperature tightly closed to protect from humidity

Inactive ingredients:

aspartame, citric acid, FD&C yellow 6, maltodextrin, natural and artificial orange flavor, silica.

Questions or comments?

1-866-467-2748

PRINCIPAL DISPLAY PANEL

CAREONE™

NDC# 41520-515-14

Compare to the fiber content in Metamucil®4 in 1 MultiHealth Fiber!™*

FIBER SUPPLEMENT POWDER

Psyllium Husk Fiber

Orange Flavored

NATURALLY AND ARTIFICIALLY FLAVORED

- HELPS LOWER CHOLESTEROLTO PROMOTE HEART HEALTH†
- BULK FORMING LAXATIVE/DIETARY FIBER SUPPLEMENT

Sugar Free not a low calorie food.

114 teaspoon doses‡

NET WT 23.3 OZ (1 LB 7.3 OZ) 660 g

OUR PHARMACISTS RECOMMEND

114 DOSE‡

Packaged by weight, not volume. Content may settle during shipping and handling.

†See back for information about soluble fiber and heart disease.

‡Serving size varies. See DIRECTIONS on back panel for more information

**THESE STATEMENTS HAVE NOT BEEN EVALUATED BY THE FOOD AND DRUG ADMINISTRATION. THIS PRODUCT IS NOT INTENDED TO DIAGNOSE, TREAT, CURE OR PREVENT ANY DISEASE.

*This product is not manufactured or distributed by Procter & Gamble, the distributor of Metamucil ®. 4 in 1 MultiHealth Fiber! ™.

TAMPER EVIDENT: DO NOT USE IF PRINTED INNER SEAL UNDER CAP IS BROKEN OR MISSING

GLUTEN FREE (may contain trace amounts less than 20 ppm). If you have specific dietary needs, you should consult your doctor before consuming this product.

This product has a low glycemic index, a measure of the effect of dietary carbohydrates on blood sugar levels.

DISTRIBUTED BY

FOODHOLD, U.S.A., LLC

LANDOVER, MD 20785

1-877-846-9949

© 2018 S&S Brands, LLC

Quality guaranteed or your money back

Package Label 114 Teaspoons Doses